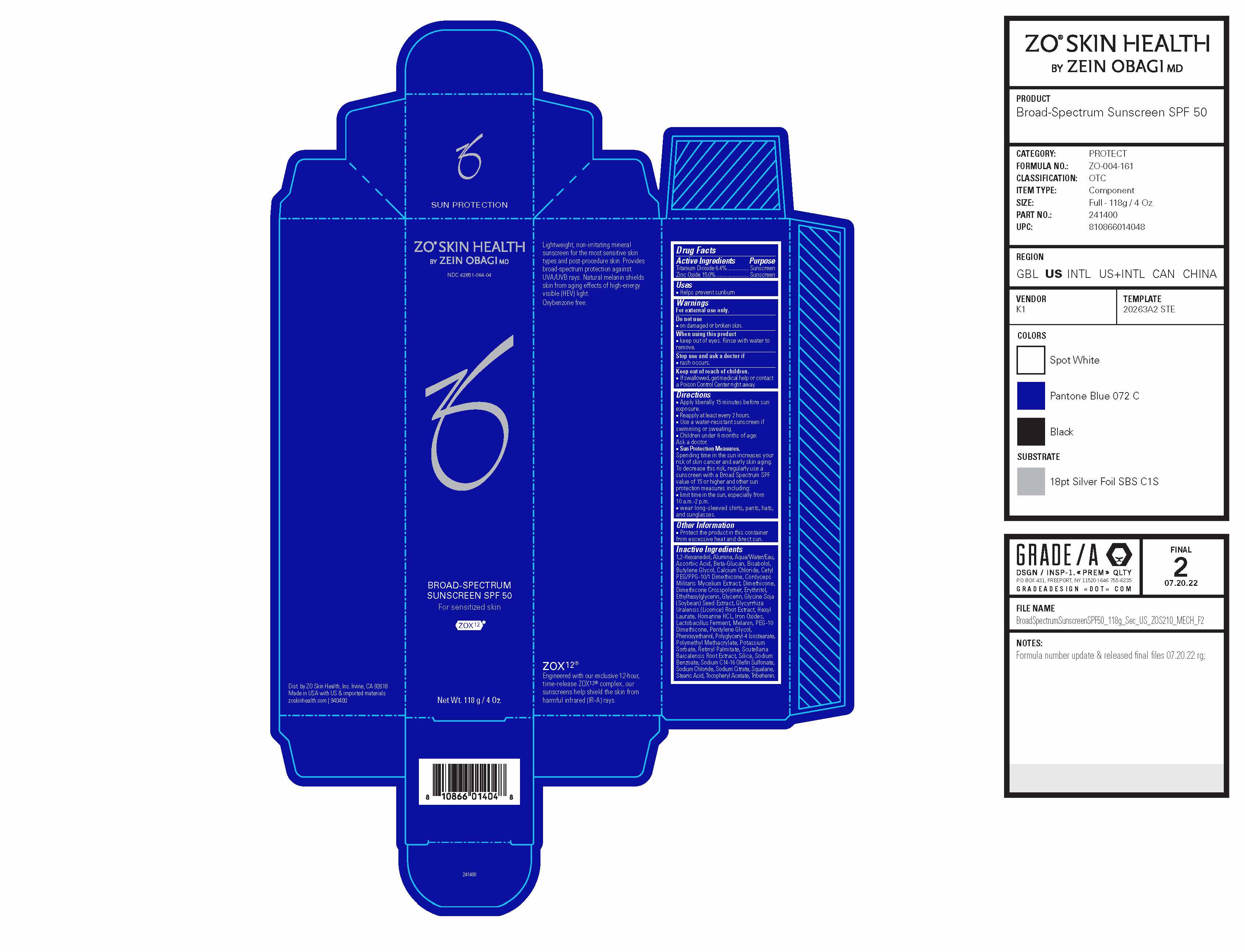 DRUG LABEL: ZO Skin Health Broad-Spectrum Sunscreen SPF 50
NDC: 42851-064 | Form: CREAM
Manufacturer: ZO Skin Health, Inc.
Category: otc | Type: HUMAN OTC DRUG LABEL
Date: 20241029

ACTIVE INGREDIENTS: TITANIUM DIOXIDE 7.552 mg/118 g; ZINC OXIDE 17.7 mg/118 g
INACTIVE INGREDIENTS: PHENOXYETHANOL; SILICON DIOXIDE; 1,2-HEXANEDIOL; ALUMINUM OXIDE; WATER; DIMETHICONE CROSSPOLYMER (450000 MPA.S AT 12% IN CYCLOPENTASILOXANE); ERYTHRITOL; ETHYLHEXYLGLYCERIN; HEXYL LAURATE; GLYCYRRHIZA URALENSIS ROOT; BUTYLENE GLYCOL; GLYCERIN; ASCORBIC ACID; CALCIUM CHLORIDE; DIMETHICONE; HOMARINE HYDROCHLORIDE; POLYGLYCERYL-4 ISOSTEARATE; VITAMIN A PALMITATE; SOLANUM ANOMALUM WHOLE; SODIUM C14-16 OLEFIN SULFONATE; SODIUM CHLORIDE; SODIUM CITRATE; SODIUM BENZOATE; POLY(METHYL METHACRYLATE; 450000 MW); POTASSIUM SORBATE; FERRIC OXIDE RED; SCUTELLARIA LATERIFLORA TOP; STEARIC ACID; SQUALANE; .ALPHA.-TOCOPHEROL ACETATE; LEVOMENOL; PENTYLENE GLYCOL; CETYL PEG/PPG-10/1 DIMETHICONE (HLB 2); TRIBEHENIN

ZO® Skin Health Broad-Spectrum Sunscreen SPF 50
42851-064

Drug Facts

Active Ingredients

Active Ingredient | Purpose
Titanium Dioxide 6.4% | Sunscreen
Zinc Oxide 15.0% | Sunscreen

Uses

- Helps prevent sunburn

Warnings

For external use only.

Do not use

- on damaged or broken skin.

When using this product

- keep out of eyes. Rinse with water to remove.

Stop use and ask a doctor if

- rash occurs.

Keep out of reach of children.

- If swallowed, get medical help or contact a Poison Control Center right away.

Directions

- Apply liberally 15 minutes before sun exposure.
- Reapply at least every 2 hours.
- Use a water-resistant sunscreen if swimming or sweating.
- Children under 6 months of age: Ask a doctor.
- Sun Protection Measures. Spending time in the sun increases your risk of skin cancer and early skin aging. To decrease this risk, regularly use a sunscreen with a Broad Spectrum SPF value of 15 or higher and other sun protection measures including: ■ limit time in the sun, especially from 10 a.m.-2 p.m. ■ wear long-sleeved shirts, pants, hats,
  and sunglasses.

Other Information

- Protect the product in this container from excessive heat and direct sun.

Inactive Ingredients

1,2-Hexanediol, Alumina, Aqua/Water/Eau, Ascorbic Acid, Beta-Glucan, Bisabolol, Butylene Glycol, Calcium Chloride, Cetyl PEG/PPG-10/1 Dimethicone, Cordyceps Militaris Mycelium Extract, Dimethicone, Dimethicone Crosspolymer, Erythritol, Ethylhexylglycerin, Glycerin, Glycine Soja (Soybean) Seed Extract, Glycyrrhiza Uralensis (Licorice) Root Extract, Hexyl Laurate, Homarine HCL, Iron Oxides, Lactobacillus Ferment, Melanin, PEG-10 Dimethicone, Pentylene Glycol, Phenoxyethanol, Polyglyceryl-4 Isostearate, Polymethyl Methacrylate, Potassium Sorbate, Retinyl Palmitate, Scutellaria Baicalensis Root Extract, Silica, Sodium Benzoate, Sodium C14-16 Olefin Sulfonate, Sodium Chloride, Sodium Citrate, Squalane, Stearic Acid, Tocopheryl Acetate, Tribehenin.

Outer Package Label

ZO® Skin Health

by ZEIN OBAGI MD

NDC 42851-064-04

BROAD-SPECTRUM
SUNSCREEN SPF 50
For sensitized skin

ZOX12®

Lightweight, non-irritating mineral sunscreen for the most sensitive skin types and post-procedure skin. Provides broad-spectrum protection against UVA/UVB rays. Natural melanin shields skin from aging effects of high-energy visible (HEV) light. Oxybenzone free.

ZOX12®

Engineered with our exclusive 12-hour, time-release ZOX12® complex, our sunscreens help shield the skin from harmful infrared (IR-A) rays.

Dist. by ZO Skin Health, Inc. Irvine, CA 92618
Made in USA with US & imported materials
zoskinhealth.com